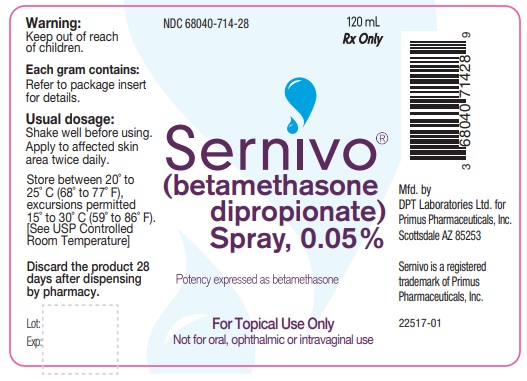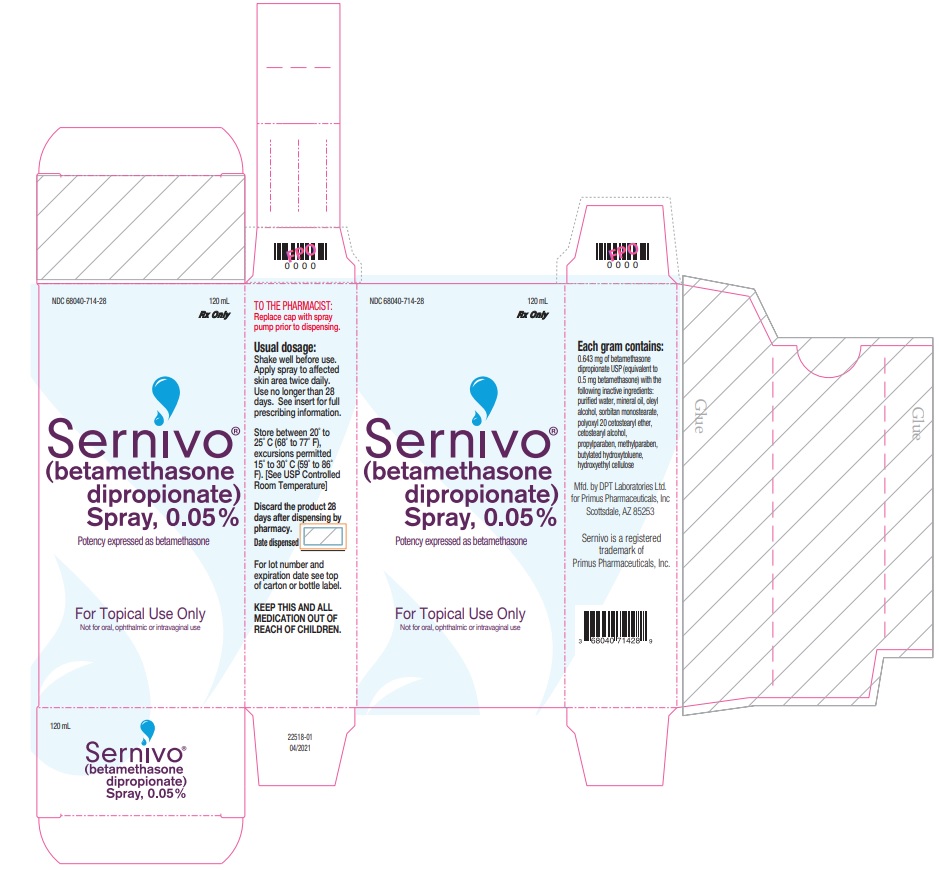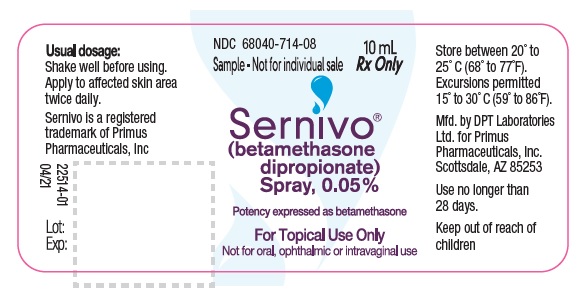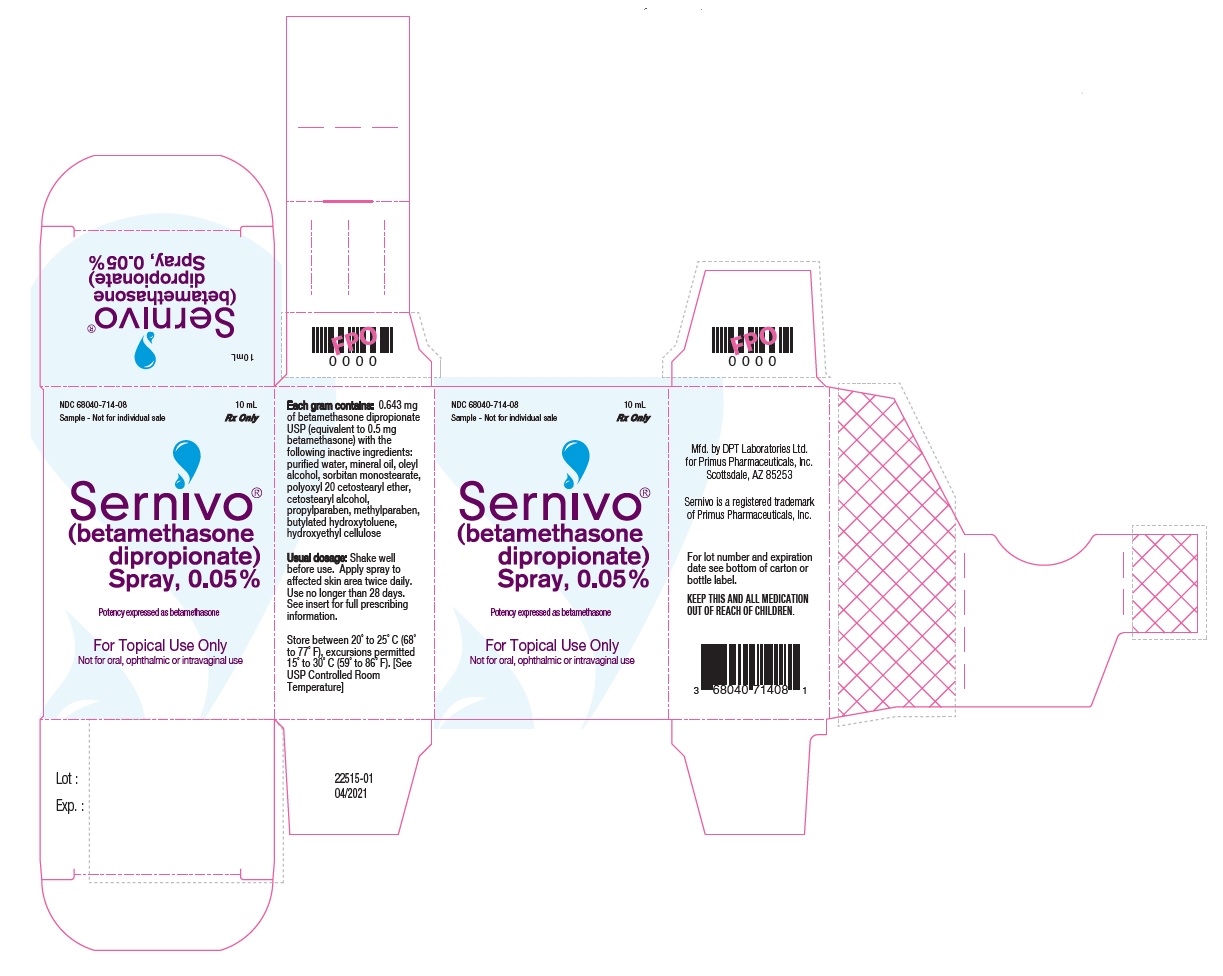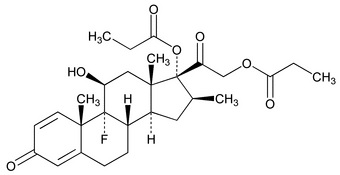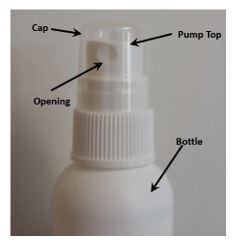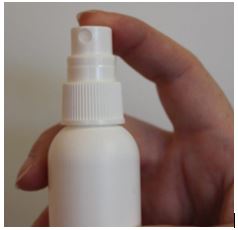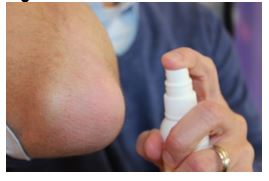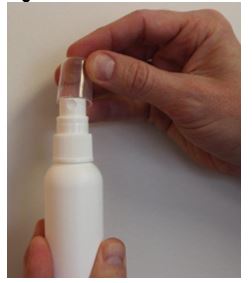 DRUG LABEL: Sernivo
NDC: 68040-714 | Form: Spray
Manufacturer: Primus Pharmaceuticals, Inc.
Category: prescription | Type: HUMAN PRESCRIPTION DRUG LABEL
Date: 20240130

ACTIVE INGREDIENTS: BETAMETHASONE DIPROPIONATE 0.5 mg/1 g
INACTIVE INGREDIENTS: BUTYLATED HYDROXYTOLUENE; CETOSTEARYL ALCOHOL; HYDROXYETHYL CELLULOSE, UNSPECIFIED; METHYLPARABEN; MINERAL OIL; OLEYL ALCOHOL; POLYOXYL 20 CETOSTEARYL ETHER; PROPYLPARABEN; WATER; SORBITAN MONOSTEARATE

HIGHLIGHTS OF PRESCRIBING INFORMATION

These highlights do not include all the information needed to use SERNIVO™ Spray safely and effectively. See full prescribing information for SERNIVO™ Spray.
SERNIVO™ (betamethasone dipropionate) spray, for topical use
Initial U.S. Approval: 1975

1 INDICATIONS AND USAGE

SERNIVO Spray is a corticosteroid indicated for the treatment of mild to moderate plaque psoriasis in patients 18 years of age or older. (1)

2 DOSAGE AND ADMINISTRATION

- Apply to the affected skin areas twice daily. Rub in gently. (2)
- Use SERNIVO Spray for up to 4 weeks and not beyond. (2)
- Discontinue treatment when control is achieved. (2)
- Do not use if atrophy is present at the treatment site. (2)
- Do not use with occlusive dressings unless directed by a physician. (2)
- Avoid use on the face, scalp, axilla, groin, or other intertriginous areas. (2)
- Not for oral, ophthalmic, or intravaginal use. (2)

3 DOSAGE FORMS AND STRENGTHS

Spray: 0.05% (equivalent to 0.5 mg betamethasone/g) (3)

4 CONTRAINDICATIONS

- None (4)

5 WARNINGS AND PRECAUTIONS

- SERNIVO Spray can produce reversible HPA axis suppression with the potential for glucocorticosteroid insufficiency during or after treatment. High potency corticosteroids, large treatment surface areas, prolonged use, use of occlusive dressings, altered skin barrier, liver failure and use in pediatric patients may predispose to HPA axis suppression. Use of topical corticosteroids may require periodic evaluation for HPA axis suppression. Modify use if HPA axis suppression develops. (5.1) High potency corticosteroids, large treatment surface areas, prolonged use, use of occlusive dressings, altered skin barrier, liver failure and young age may predispose to HPA axis suppression. (5.1)
- Topical corticosteroids may increase the risk of cataracts and glaucoma. If visual symptoms occur, consider referral to an ophthalmologist. (5.2)

6 ADVERSE REACTIONS

The most common adverse reactions (≥1%) are application site reactions, including pruritus, burning and/or stinging, pain, and atrophy. (6.1)

To report SUSPECTED ADVERSE REACTIONS, contact Promius Pharma, LLC. at 1-888-966-8766 or FDA at 1-800-FDA-1088 or www.fda.gov/medwatch.

FULL PRESCRIBING INFORMATION

1 INDICATIONS AND USAGE

SERNIVO Spray is indicated for the treatment of mild to moderate plaque psoriasis in patients 18 years of age or older.

2 DOSAGE AND ADMINISTRATION

Shake well before use.

Apply SERNIVO Spray to the affected skin areas twice daily and rub in gently.

Use SERNIVO Spray for up to 4 weeks of treatment. Treatment beyond 4 weeks is not recommended.

Discontinue SERNIVO Spray when control is achieved.

Do not use if atrophy is present at the treatment site.

Do not bandage, cover, or wrap the treated skin area unless directed by a physician.

Avoid use on the face, scalp, axilla, groin, or other intertriginous areas.

SERNIVO Spray is for topical use only. It is not for oral, ophthalmic, or intravaginal use.

3 DOSAGE FORMS AND STRENGTHS

Spray, 0.05% for topical use. Each gram of SERNIVO Spray contains 0.643 mg betamethasone dipropionate USP (equivalent to 0.5 mg betamethasone) in a slightly thickened, white to off-white oil-in-water emulsion.

4 CONTRAINDICATIONS

None.

5 WARNINGS AND PRECAUTIONS

5.1 Effects on Endocrine System

SERNIVO Spray can produce reversible hypothalamic-pituitary-adrenal (HPA) axis suppression with the potential for glucocorticosteroid insufficiency. This may occur during or after withdrawal of treatment. Factors that predispose to HPA axis suppression include the use of high-potency corticosteroids, large treatment surface areas, prolonged use, use of occlusive dressings, altered skin barrier, liver failure, and young age.

Evaluation for HPA axis suppression may be done by using the adrenocorticotropic hormone (ACTH) stimulation test.

In a study including 48 evaluable subjects 18 years of age or older with moderate to severe plaque psoriasis, abnormal ACTH stimulation test results suggestive of adrenal suppression were identified in 5 out of 24 (20.8%) subjects after treatment with SERNIVO Spray twice daily for 15 days. No subject (0 out of 24) had abnormal ACTH stimulation test results after treatment with SERNIVO Spray twice daily for 29 days [see Clinical Pharmacology (12.2)].

If HPA axis suppression is documented, gradually withdraw the drug, reduce the frequency of application, or substitute with a less potent corticosteroid. If signs and symptoms of steroid withdrawal occur, supplemental systemic corticosteroids may be required.

Systemic effects of topical corticosteroids may also manifest as Cushing’s syndrome, hyperglycemia, and glucosuria. These events are rare and generally occur after prolonged exposure to larger than recommended doses, particularly with high-potency topical corticosteroids.

Minimize the unwanted risks from endocrine effects by mitigating the risk factors favoring increased systemic bioavailability and by using the product as recommended [see Dosage and Administration (2)].

Pediatric patients may be more susceptible to systemic toxicity due to their larger skin surface to body mass ratios. Use of SERNIVO Spray is not recommended in pediatric patients [see Use in Specific Populations (8.4)].

5.2 Ophthalmic Adverse Reactions

Use of topical corticosteroids, including SERNIVO Spray, may increase the risk of posterior subcapsular cataracts and glaucoma. Cataracts and glaucoma have been reported postmarketing with the use of topical corticosteroid products, including betamethasone dipropionate [see Adverse Reactions (6.2)].

Avoid contact of SERNIVO Spray with eyes. Advise patients to report any visual symptoms and consider referral to an ophthalmologist for evaluation.

5.3 Allergic Contact Dermatitis

Allergic contact dermatitis with corticosteroids is usually diagnosed by observing failure to heal rather than noting a clinical exacerbation. Corroborate such an observation with appropriate diagnostic patch testing. If irritation develops, discontinue the topical corticosteroid and institute appropriate therapy.

6 ADVERSE REACTIONS

6.1 Clinical Trials Experience

Because clinical trials are conducted under widely varying conditions, adverse reaction rates observed in the clinical trials of a drug cannot be directly compared to rates in the clinical trials of another drug and may not reflect the rates observed in clinical practice.

In two randomized, multicenter, prospective vehicle-controlled clinical trials, subjects with moderate plaque psoriasis of the body applied SERNIVO Spray or vehicle spray twice daily for 4 weeks. A total of 352 subjects applied SERNIVO Spray and 180 subjects applied vehicle spray.

Adverse reactions that occurred in at least 1% of subjects treated with SERNIVO Spray for up to 28 days are presented in Table 1.

Table 1: Adverse Reactions Occurring in ≥1% of Subjects Treated with SERNIVO Spray for up to Four Weeks
 | SERNIVO Spray b.i.d. (N=352) | Vehicle Spray b.i.d. (N=180)
Application site pruritus | 6.0% | 9.4%
Application site burning and/or stinging | 4.5% | 10.0%
Application site pain | 2.3% | 3.9%
Application site atrophy | 1.1% | 1.7%

Less common adverse reactions (with occurrence lower than 1% but higher than 0.1%) in subjects treated with SERNIVO Spray were application site reactions including telangiectasia, dermatitis, discoloration, folliculitis and skin rash, in addition to dysgeusia and hyperglycemia. These adverse reactions were not observed in subjects treated with vehicle.

6.2 Postmarketing Experience

Because adverse reactions are reported voluntarily from a population of uncertain size, it is not always possible to reliably estimate their frequency or establish a causal relationship to drug exposure.

Postmarketing reports for local adverse reactions to topical corticosteroids have also included striae, irritation, dryness, acneiform eruptions, hypopigmentation, perioral dermatitis, allergic contact dermatitis, secondary infection, hypertrichosis, and miliaria.

Hypersensitivity reactions, consisting of predominantly skin signs and symptoms, e.g., contact dermatitis, pruritus, bullous dermatitis, and erythematous rash have been reported.

Ophthalmic adverse reactions of cataracts, glaucoma, and increased intraocular pressure have been reported with the use of topical corticosteroids, including topical betamethasone products.

8 USE IN SPECIFIC POPULATIONS

8.1 Pregnancy

There are no available data on SERNIVO Spray use in pregnant women to evaluate a drug-associated risk of major birth defects, miscarriage, or adverse maternal or fetal outcomes.

Observational studies suggest an increased risk of low birthweight infants with the use of greater than 300 grams of potent or very potent topical corticosteroid during a pregnancy. Advise pregnant women that SERNIVO Spray may increase the risk of having a low birthweight infant and to use SERNIVO Spray on the smallest area of skin and for the shortest duration possible.

In animal reproduction studies, increased malformations, including umbilical hernias, cephalocele, and cleft palate, were observed after intramuscular administration of betamethasone dipropionate to pregnant rabbits during the period of organogenesis (see Data). The available data do not allow the calculation of relevant comparisons between the systemic exposure of betamethasone dipropionate observed in animal studies to the systemic exposure that would be expected in humans after topical use of SERNIVO Spray.

The estimated background risk of major birth defects and miscarriage for the indicated population is unknown. All pregnancies have a background risk of birth defect, loss, or other adverse outcomes. In the U.S. general population, the estimated risk of major birth defects and miscarriage in clinically recognized pregnancies is 2 to 4% and 15 to 20%, respectively.

Data

Animal Data

Administration of 0.05 mg/kg betamethasone dipropionate intramuscularly to pregnant rabbits during the period of organogenesis caused malformations. The abnormalities observed included umbilical hernias, cephalocele, and cleft palate.

8.2 Lactation

Risk Summary

There are no data regarding the presence of betamethasone dipropionate in human milk, the effects on the breastfed infant, or the effects on milk production after topical application of SERNIVO Spray to women who are breastfeeding.

It is possible that topical administration of betamethasone dipropionate could result in sufficient systemic absorption to produce detectable quantities in human milk. The developmental and health benefits of breastfeeding should be considered along with the mother’s clinical need for SERNIVO Spray and any potential adverse effects on the breastfed infant from SERNIVO Spray or from the underlying maternal condition.

Clinical Considerations

To minimize potential exposure to the breastfed infant via breast milk, use SERNIVO Spray on the smallest area of skin and for the shortest duration possible while breastfeeding. Advise breastfeeding women not to apply SERNIVO Spray directly to the nipple and areola to avoid direct infant exposure [see Use in Specific Populations (8.4)].

8.4 Pediatric Use

Safety and effectiveness of SERNIVO Spray in patients younger than 18 years of age have not been studied, therefore use in pediatric patients is not recommended. Because of a higher ratio of skin surface area to body mass, pediatric patients are at greater risk of systemic toxicity, including HPA axis suppression and adrenal insufficiency, when treated with topical drugs. [see Warnings and Precautions (5.1)]

Rare systemic effects such as Cushing's syndrome, linear growth retardation, delayed weight gain, and intracranial hypertension have been reported in pediatric patients, especially those with prolonged exposure to large doses of high potency topical corticosteroids.

Local adverse reactions including skin atrophy have also been reported with use of topical corticosteroids in pediatric patients.

8.5 Geriatric Use

Clinical studies of SERNIVO Spray did not include sufficient numbers of subjects who were 65 years of age or older to determine whether they respond differently from younger subjects.

11 DESCRIPTION

SERNIVO Spray contains 0.0643% betamethasone dipropionate (equivalent to 0.05% betamethasone), a synthetic, fluorinated corticosteroid for topical use.

The chemical name for betamethasone dipropionate is 9-fluoro-11(β), 17, 21-trihydroxy-16(β)-methylpregna-1,4-diene-3,20-dione-17,21-dipropionate. The empirical formula is C28H37FO7 and the molecular weight is 504.6. The structural formula is shown below.

Each gram of SERNIVO Spray contains 0.643 mg of betamethasone dipropionate USP (equivalent to 0.5 mg betamethasone) in a slightly thickened, white to off-white, oil-in-water, non-sterile emulsion with the following inactive ingredients: butylated hydroxytoluene, cetostearyl alcohol, hydroxyethyl cellulose, methylparaben, mineral oil, oleyl alcohol, polyoxyl 20 cetostearyl ether, propylparaben, purified water, and sorbitan monostearate. SERNIVO Spray is co-packaged with a manual spray pump for installation by the pharmacist prior to dispensing to patients.

12 CLINICAL PHARMACOLOGY

12.1 Mechanism of Action

Corticosteroids play a role in cellular signaling, immune function, inflammation, and protein regulation; however, the precise mechanism of action of SERNIVO Spray in psoriasis is unknown.

12.2 Pharmacodynamics

Vasoconstrictor studies performed with SERNIVO Spray in healthy subjects indicate that it is in the mid-range of potency as compared with other topical corticosteroids; however, similar blanching scores do not necessarily imply therapeutic equivalence.

The potential for HPA axis suppression by SERNIVO Spray was evaluated in a study randomizing 52 adult subjects with moderate to severe plaque psoriasis. SERNIVO Spray was applied twice daily for 15 or 29 days, in subjects with psoriasis involving a mean of 29.0% and 26.5% body surface area at baseline across the 2 treatment duration arms, respectively. Forty-eight (48) subjects were evaluated for HPA axis suppression at the end of treatment. The proportion of subjects demonstrating HPA axis suppression was 20.8% (5 out of 24) in subjects treated with SERNIVO Spray for 15 days. No subjects (0 out of 24) treated with SERNIVO Spray for 29 days had HPA axis suppression. In this study HPA axis suppression was defined as serum cortisol level ≤18 mcg/dL 30-minutes post-cosyntropin stimulation. In the 4 subjects with available follow-up values, all subjects had normal ACTH stimulation tests at follow-up.

12.3 Pharmacokinetics

The extent of percutaneous absorption of topical corticosteroids is determined by many factors including the vehicle, the integrity of the epidermal barrier, and the use of occlusive dressings.

Topical corticosteroids are absorbed through normal intact skin. Inflammation and/or other disease processes in the skin may increase percutaneous absorption.

Plasma concentrations of betamethasone dipropionate, betamethasone-17-propionate, and betamethasone were measured at baseline, and before and after the last dose (1, 3, and 6 hours) in the HPA axis suppression trial in subjects with psoriasis [see Clinical Pharmacology (12.2)]. The majority of subjects had no measurable plasma concentration (<5.00 pg/mL) of betamethasone dipropionate, while the metabolites, betamethasone-17-propionate and betamethasone, were detected in the majority of subjects (Table 2). There was high variability in the data but there was a trend toward higher systemic exposure at Day 15 and lower systemic exposure at Day 29.

Table 2: Mean (±SD) Maximum Plasma Concentrations (pg/mL) of Betamethasone Dipropionate Metabolites after 15 or 29 Days of Treatment with SERNIVO Spray
Analyte (pg/mL) | SERNIVO Spray b.i.d. (15 days) | SERNIVO Spray b.i.d. (29 days)
Betamethasone-17-propionate | 120 ± 127 | 63.9 ± 52.6
Betamethasone | 119 ± 176 | 57.6 ± 55.9

13 NONCLINICAL TOXICOLOGY

13.1 Carcinogenesis, Mutagenesis, Impairment of Fertility

Long-term animal studies have not been performed to evaluate the carcinogenic potential of betamethasone dipropionate.

In a 90-day repeat-dose toxicity study in rats, topical administration of betamethasone dipropionate spray formulation at dose concentrations of 0.05% and 0.1% (providing dose levels up to 0.5 mg/kg/day in males and 0.25 mg/kg/day in females) resulted in a toxicity profile consistent with long-term exposure to corticosteroids including reduced body weight gain, adrenal atrophy, and histological changes in bone marrow, thymus and spleen indicative of severe immune suppression. A no observable adverse effect level (NOAEL) could not be determined in this study. Although the clinical relevance of the findings in animals to humans is not clear, sustained glucocorticoid-related immune suppression may increase the risk of infection and possibly the risk of carcinogenesis.

Betamethasone was negative in the bacterial mutagenicity assay (Salmonella typhimurium and Escherichia coli), and in the mammalian cell mutagenicity assay (CHO/HGPRT). It was positive in the in vitro human lymphocyte chromosome aberration assay, and equivocal in the in vivo mouse bone marrow micronucleus assay.

Studies in rabbits, mice, and rats using intramuscular doses up to 1, 33, and 2 mg/kg, respectively, resulted in dose-related increases in fetal resorptions in rabbits and mice.

14 CLINICAL STUDIES

Two multi-center, randomized, double-blind, vehicle-controlled clinical trials were conducted in subjects aged 18 years and older with moderate plaque psoriasis. In both trials, randomized subjects applied SERNIVO Spray or vehicle spray to the affected areas twice daily for 28 days. Enrolled subjects had body surface area of involvement between 10% to 20%, and an Investigator Global Assessment (IGA) score of 3 (moderate).

Efficacy was assessed as the proportion of subjects who were considered a treatment success (defined as having an IGA score of 0 or 1 [clear or almost clear] and at least a 2-grade reduction from baseline). Table 3 presents the efficacy results at Day 15 and Day 29.

Table 3: Proportion of Subjects with Plaque Psoriasis with Treatment Successa after 14 Days and 28 Days of Treatment
 | Study 1 |  | Study 2
 | SERNIVO Spray b.i.d. (N=182) | Vehicle Spray b.i.d. (N=95) | SERNIVO Spray b.i.d. (N=174) | Vehicle Spray b.i.d. (N=87)
Treatment Success at Day 15 | 21.5% | 7.4% | 19.0% | 2.3%
Treatment Success at Day 29 | 42.7% | 11.7% | 34.5% | 13.6%
a Treatment success is defined as an IGA of 0 or 1 (clear or almost clear) and at least a 2-grade reduction from baseline.

16 HOW SUPPLIED/STORAGE AND HANDLING

16.1 How Supplied/Storage

SERNIVO Spray is a slightly thickened, white to off-white, non-sterile emulsion supplied in high density polyethylene bottles with a heat induction seal lined polypropylene cap. The drug is supplied in the following volumes:

- 120 mL (NDC 68040-714-28)

Store at controlled room temperature of 20°C to 25°C (68°F to 77°F), excursions permitted to 15°C to 30°C (59°F to 86°F) [See USP Controlled Room Temperature].

Each unit is co-packaged with a manual spray pump for installation by the pharmacist prior to dispensing.

16.2 Handling/Instructions for the Pharmacist

1. Remove the spray pump from the wrapper.
2. Remove and discard the cap from the bottle.
3. Keeping the bottle upright, insert the spray pump into the bottle and turn clockwise until it is closed tightly.
4. Dispense the bottle with the spray pump inserted.
5. Include the date dispensed in the space provided on the carton.

17 PATIENT COUNSELING INFORMATION

Advise the patient to read the FDA-approved patient labeling (Patient Information and Instructions for Use).

Inform patients of the following:

- Discontinue therapy when control is achieved, unless directed otherwise by the physician.
- Do not use for longer than 4 consecutive weeks.
- Avoid contact with the eyes.
- Avoid use of SERNIVO Spray on the face, scalp, underarms, groin or other intertriginous areas, unless directed by the physician.
- Do not occlude the treatment area with bandage or other covering, unless directed by the physician.
- Local reactions and skin atrophy are more likely to occur with occlusive use, prolonged use, or use of higher potency corticosteroids.
- Advise a woman to use SERNIVO Spray on the smallest area of skin and for the shortest duration possible while pregnant or breastfeeding. Advise breastfeeding women not to apply SERNIVO Spray directly to the nipple and areola to avoid direct infant exposure.

Manufactured by: DPT Laboratories, Ltd., San Antonio, TX 78215

For Encore Dermatology, Inc. Scottsdale, AZ 85254

Sernivo is a registered trademark of Encore Dermatology, Inc.

Revised: 2021-04

Product Insert Item Number SER1325 03/20

PATIENT INFORMATION

SERNIVO™ (ser-ne-vo)
(betamethasone dipropionate)
Spray, 0.05%

Important: SERNIVO Spray is for use on the skin only. Do not get SERNIVO Spray near or in your eyes, mouth, or vagina.

What is SERNIVO Spray?

- SERNIVO Spray is a prescription corticosteroid medicine used to treat mild to moderate plaque psoriasis in people 18 years of age and older.

It is not known if SERNIVO Spray is safe and effective in children under 18 years of age. SERNIVO Spray is not recommended for use in patients under 18 years of age.

Before you use SERNIVO Spray, tell your doctor about all of your medical conditions, including if you:

- are allergic to any of the ingredients in SERNIVO Spray. See the end of this leaflet for a list of the ingredients in SERNIVO Spray.
- have thinning of the skin (atrophy) at the treatment site
- are pregnant or plan to become pregnant. It is not known if SERNIVO Spray will harm your unborn baby.
- are breastfeeding or plan to breastfeed. It is not known if SERNIVO Spray passes into breast milk.

Tell your doctor about all the medicines you take, including prescription and over-the-counter medicines, vitamins, and herbal supplements. Especially tell your doctor if you take other corticosteroid medicines by mouth or use other products on your skin that contain corticosteroids.

How should I use SERNIVO Spray?

See the “Instructions for Use” for detailed information about the right way to apply SERNIVO Spray.

- Use SERNIVO Spray exactly as your doctor tells you to use it.
- Your doctor should tell you how much SERNIVO Spray to use and where to apply it.
- Apply SERNIVO Spray 2 times a day.
- Use SERNIVO Spray for the shortest amount of time needed to treat your plaque psoriasis. Tell your doctor if your skin condition is not getting better after 4 weeks of using SERNIVO Spray. Do not use SERNIVO Spray for longer than 4 weeks.
- Wash your hands after applying SERNIVO Spray.
- Do not use SERNIVO Spray on your face, scalp, underarms (armpits), groin, or areas where your skin may touch or rub together.
- Do not bandage, cover, or wrap the treated skin area, unless your doctor tells you to.

What are the possible side effects of SERNIVO Spray?

- SERNIVO Spray can pass through your skin. Too much SERNIVO Spray passing through your skin can cause your adrenal glands to stop working. Your doctor may do blood tests to check for adrenal gland problems.

The most common side effects of SERNIVO Spray include itching, burning, stinging, pain, and thinning of skin (atrophy) at the treated site.

These are not all the possible side effects of SERNIVO Spray.

Call your doctor for medical advice about side effects. You may report side effects to FDA at 1-800-FDA-1088.

How should I store SERNIVO Spray?

- Store SERNIVO Spray at room temperature between 68°F to 77°F (20°C to 25°C).
- Throw away (discard) any unused SERNIVO Spray after 4 weeks

Keep SERNIVO Spray and all medicines out of the reach of children.

General information about the safe and effective use of SERNIVO Spray.

Medicines are sometimes prescribed for purposes other than those listed in a Patient Information leaflet. Do not use SERNIVO Spray for a condition for which it was not prescribed. Do not give SERNIVO Spray to other people even if they have the same symptoms that you have. It may harm them. You can ask your pharmacist or doctor for information about SERNIVO Spray that is written for health professionals.

What are the ingredients in SERNIVO Spray?

Active ingredient: betamethasone dipropionate

Inactive ingredients: butylated hydroxytoluene, cetostearyl alcohol, hydroxyethyl cellulose, methylparaben, mineral oil, oleyl alcohol, polyoxyl 20 cetostearyl ether, propylparaben, purified water, and sorbitan monostearate

Manufactured by: DPT Laboratories, Ltd., San Antonio, TX 78215

Distributed by: Encore Dermatology, Inc. Scottsdale, AZ 85254
SER 1288
4/19

This Patient Information has been approved by the U.S. Food and Drug Administration.

Revised: 04/2019

Instructions for Use

SERNIVO™ (ser-ne-vo)
(betamethasone dipropionate)
Spray, 0.05%

Important: SERNIVO Spray is for use on the skin only. Do not get SERNIVO Spray near or in your eyes, mouth, or vagina.

Read this “Instructions for Use” before you start using SERNIVO Spray and each time you get a refill. There may be new information. This information does not take the place of talking with your doctor about your medical condition or treatment.

Parts of the SERNIVO Spray bottle. (See Figure A)

Figure A

How to apply SERNIVO Spray:

Step 1: Shake the SERNIVO Spray bottle well. Remove the cap from the pump top.

Step 2: Hold the bottle in an upright position while pointing the opening of the pump top in the direction of the affected area. To spray, push down on the pump top. Apply SERNIVO Spray to the affected area as instructed by your doctor. (See Figure B)

Figure B

Step 3: Spray only enough SERNIVO Spray to cover the affected area, for example, the elbow (See Figure C). Rub in SERNIVO Spray gently.

Figure C

Repeat Steps 2 and 3 to apply SERNIVO Spray to other affected areas as instructed by your doctor.

Step 4: After applying SERNIVO Spray, place the cap back onto the pump top. (See Figure D)

Figure D

How should I store SERNIVO Spray?

- Store SERNIVO Spray at room temperature between 68°F to 77°FF (20°FC to 25°C).
- Throw away (discard) any unused SERNIVO Spray after 28 days.

Keep SERNIVO Spray and all medicines out of the reach of children.

This "Instructions for Use" has been approved by the U.S. Food and Drug Administration.

Manufactured by: DPT Laboratories, Ltd., San Antonio, TX 78215
Distributed by: Encore Dermatology, Inc., Scottsdale AZ 85254

SERNIVO is a registered trademark of Encore Dermatology, Inc

Issued: 02/2016
Revised: 04/2019
SER1289
4/19

PRINCIPAL DISPLAY PANEL - NDC: 68040-714-28 - 120 mL Bottle Label

NDC 68040-714-28

120 mL

Rx Only

Sernivo®

(betamethasone dipropionate) Spray, 0.05%

Potency expressed as betamethasone

For Topical Use Only

Not for oral, ophthalmic or intravaginal use

PRINCIPAL DISPLAY PANEL - NDC: 68040-714-28 - 120 mL Carton Label

NDC 68040-714-28

120 mL

Rx Only

Sernivo®

(betamethasone dipropionate) Spray, 0.05%

Potency expressed as betamethasone

For Topical Use Only

Not for oral, ophthalmic or intravaginal use

PRINCIPAL DISPLAY PANEL - NDC: 68040-714-08 - 10 mL Sample Bottle Label

NDC 68040-714-08

Sample - Not for individual sale

10 mL

Rx Only

Sernivo®

(betamethasone dipropionate) Spray, 0.05%

Potency expressed as betamethasone

For Topical Use Only

Not for oral, ophthalmic or intravaginal use

PRINCIPAL DISPLAY PANEL - NDC: 68040-714-08 - 10 mL Sample Carton Label

NDC 68040-714-08

Sample - Not for individual sale

10 mL

Rx Only

Sernivo®

(betamethasone dipropionate) Spray, 0.05%

Potency expressed as betamethasone

For Topical Use Only

Not for oral, ophthalmic or intravaginal use